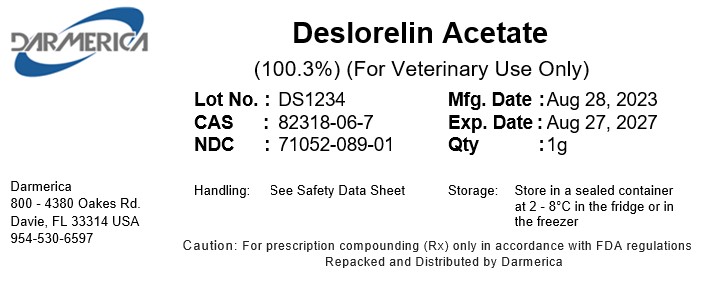 DRUG LABEL: Deslorelin Acetate
NDC: 71052-089 | Form: POWDER
Manufacturer: Darmerica LLC
Category: other | Type: BULK INGREDIENT - ANIMAL DRUG
Date: 20251002

ACTIVE INGREDIENTS: DESLORELIN 1 g/1 g

Deslorelin Acetate